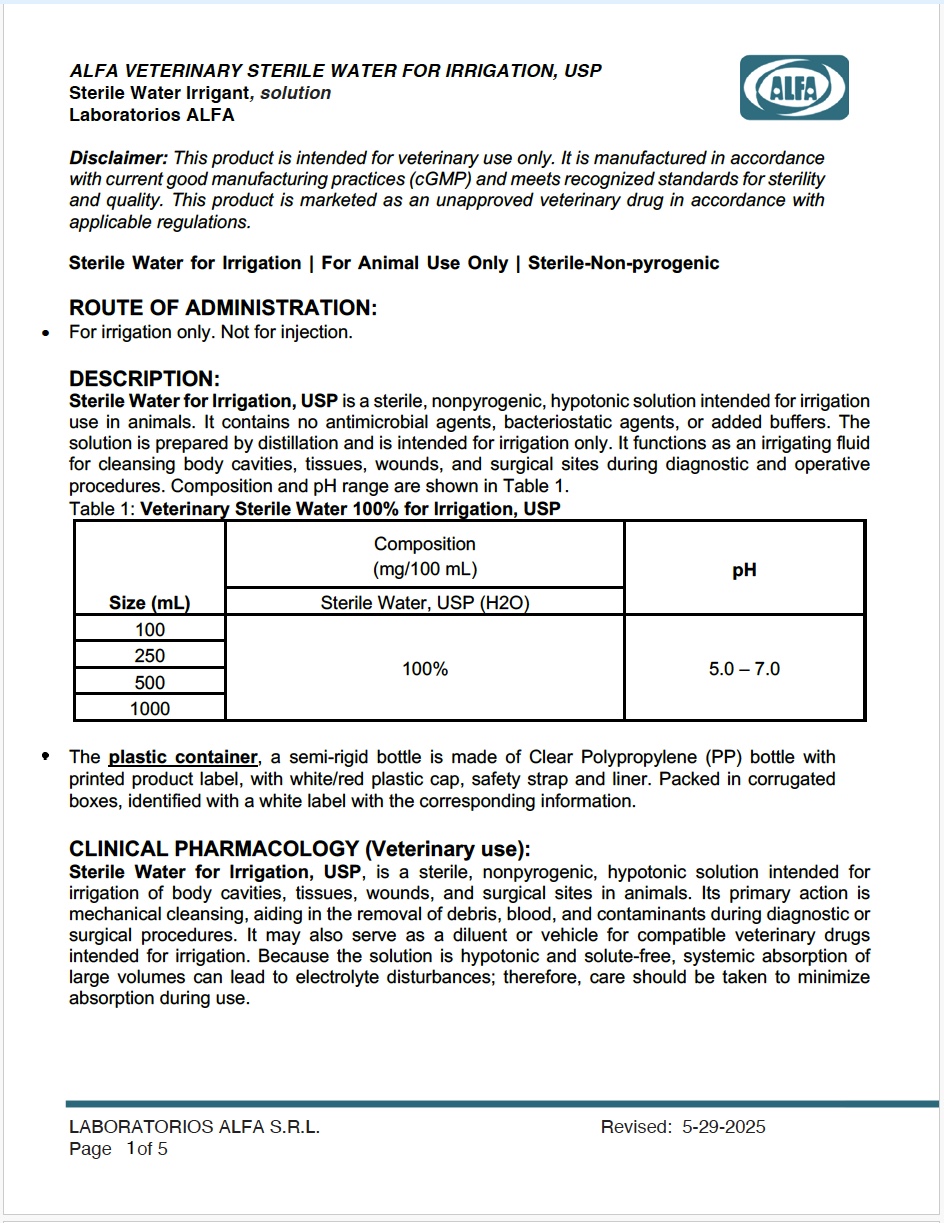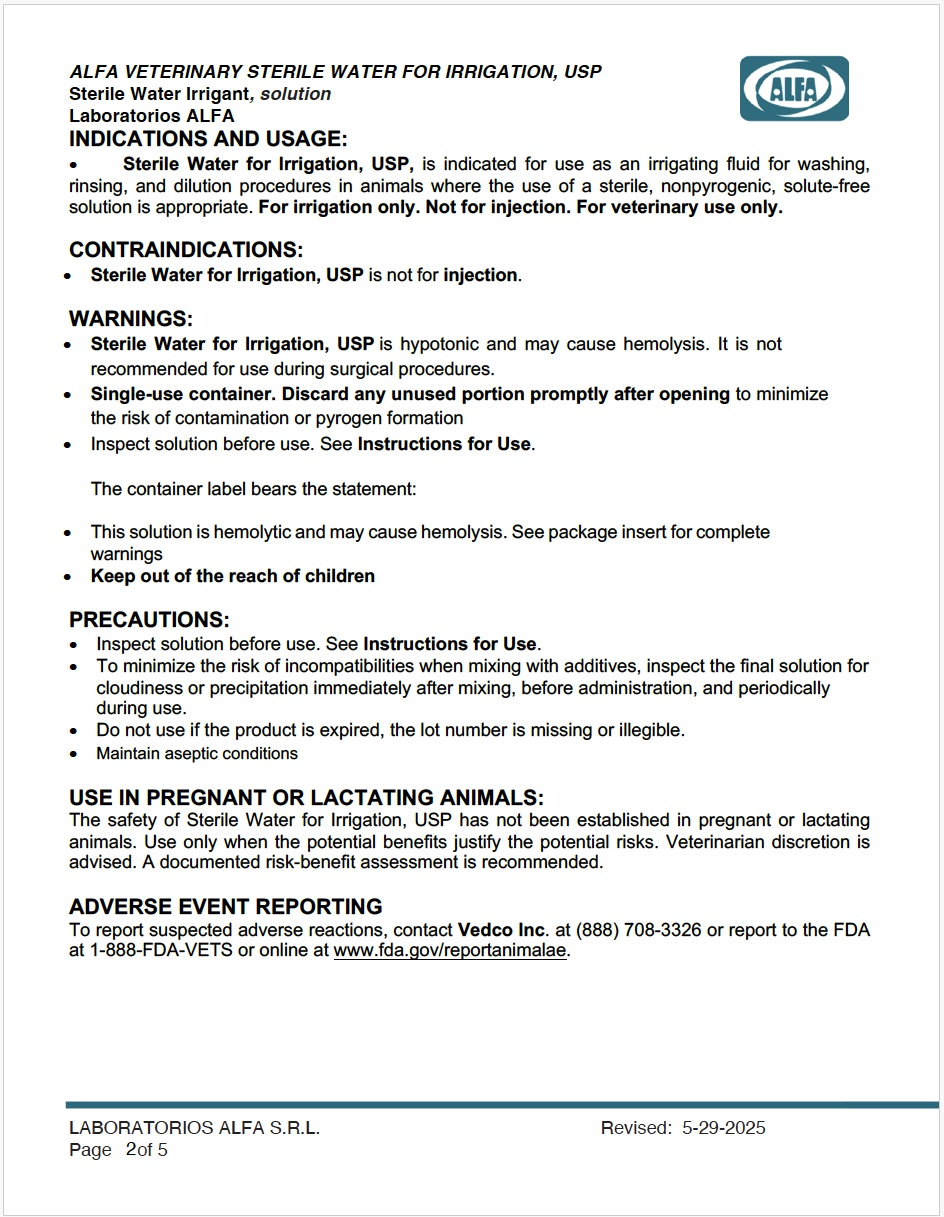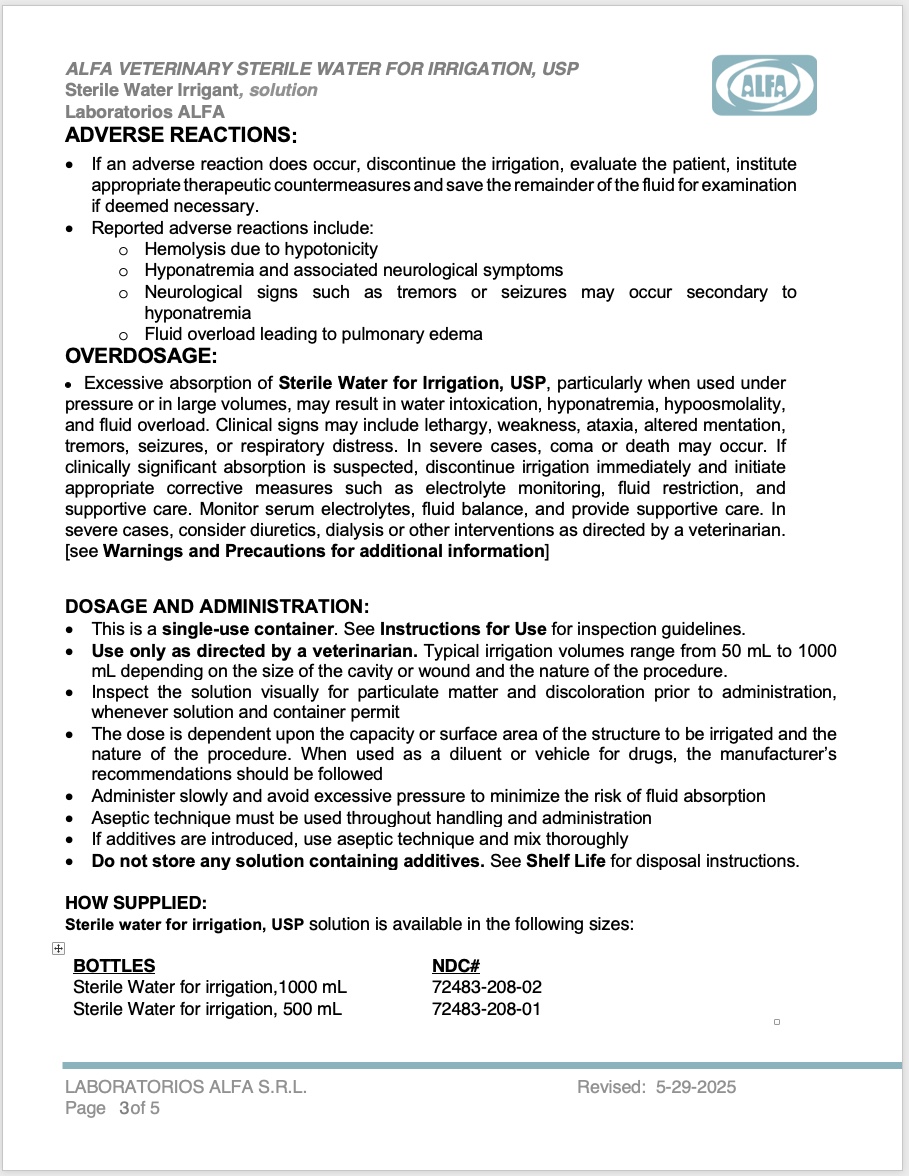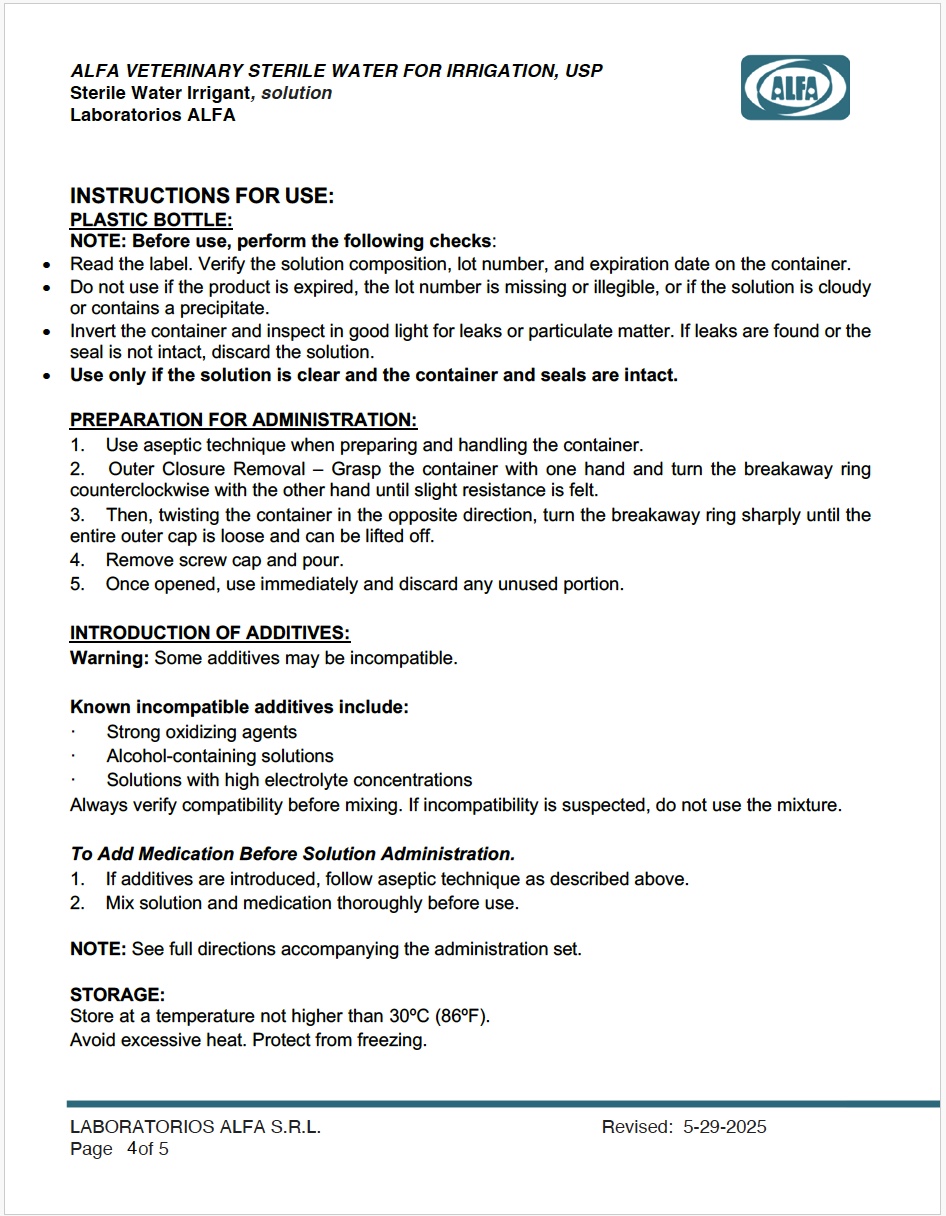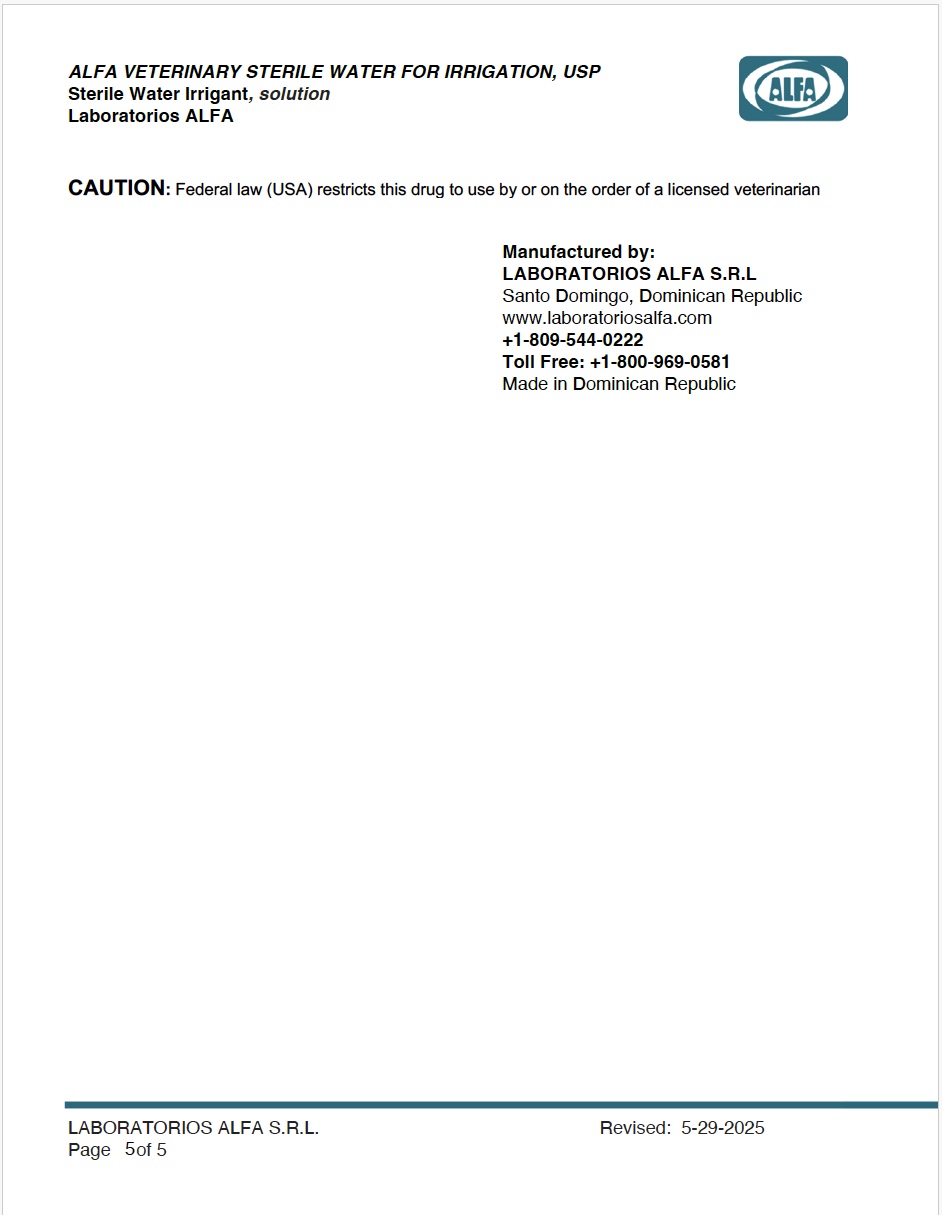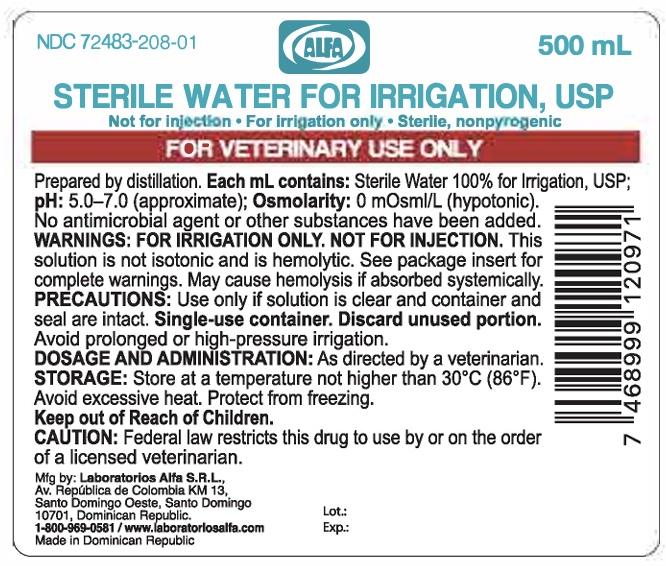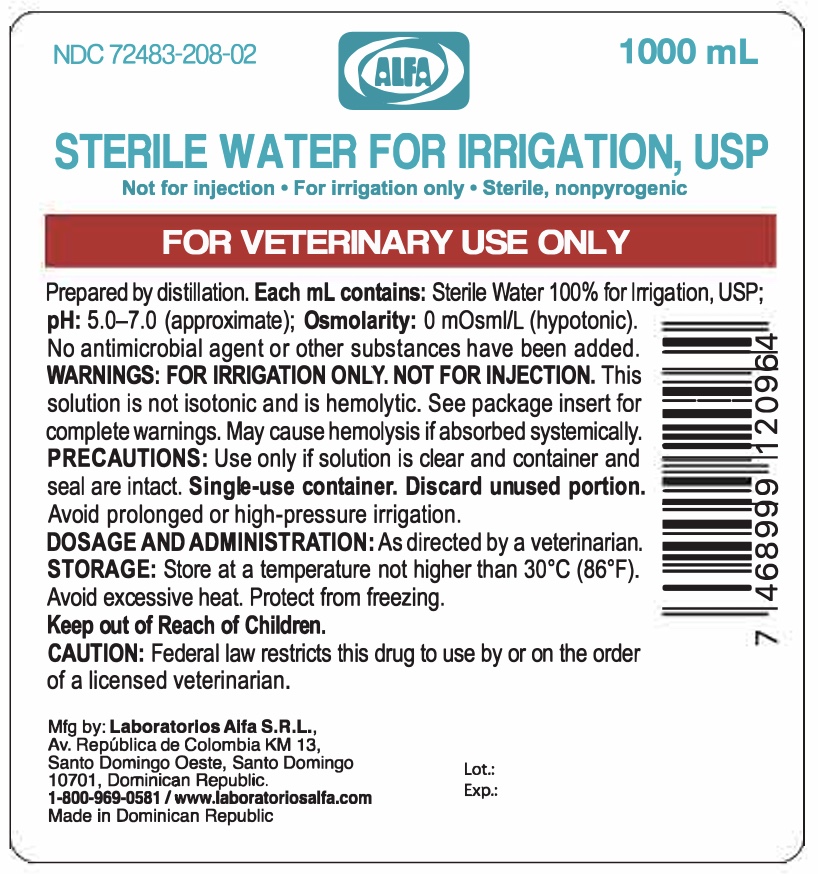 DRUG LABEL: Sterile Water for Irrigation
NDC: 72483-208 | Form: IRRIGANT
Manufacturer: Laboratorios Alfa SRL
Category: animal | Type: PRESCRIPTION ANIMAL DRUG LABEL
Date: 20260114

ACTIVE INGREDIENTS: WATER 100 mL/100 mL

DESCRIPTION

Disclaimer: This product is intended for veterinary use only. It is manufactured in accordance with current good manufacturing practices (cGMP) and meets recognized standards for sterility and quality. This product is marketed as an unapproved veterinary drug in accordance with applicable regulations.

Sterile Water for Irrigation | For Animal Use Only | Sterile-Non-pyrogenic

ROUTE OF ADMINISTRATION: For irrigation only. Not for injection.

DESCRIPTION:
Sterile Water for Irrigation, USP is a sterile, nonpyrogenic, hypotonic solution intended for irrigation use in animals. It contains no antimicrobial agents, bacteriostatic agents, or added buffers. The solution is prepared by distillation and is intended for irrigation only. It functions as an irrigating fluid for cleansing body cavities, tissues, wounds, and surgical sites during diagnostic and operative procedures. Composition and pH range are shown in Table 1.
Table 1: Veterinary Sterile Water 100% for Irrigation, USP

Size (mL) | Composition (mg/100 mL)
Size (mL) | Sterile Water | pH
100 | 100% | 5.0-7.0
250 | 100% | 5.0-7.0
500 | 100% | 5.0-7.0
1000 | 100% | 5.0-7.0

The plastic container, a semi-rigid bottle is made of Clear Polypropylene (PP) bottle with printed product label, with white/red plastic cap, safety strap and liner. Packed in corrugated boxes, identified with a white label with the corresponding information.

OTHER SAFETY INFORMATION

CAUTION: Federal law (USA) restricts this drug to use by or on the order of a licensed veterinarian.

CLINICAL PHARMACOLOGY (Veterinary use):

Sterile Water for Irrigation, USP, is a sterile, nonpyrogenic, hypotonic solution intended for irrigation of body cavities, tissues, wounds, and surgical sites in animals. Its primary action is mechanical cleansing, aiding in the removal of debris, blood, and contaminants during diagnostic or surgical procedures. It may also serve as a diluent or vehicle for compatible veterinary drugs intended for irrigation. Because the solution is hypotonic and solute-free, systemic absorption of large volumes can lead to electrolyte disturbances; therefore, care should be taken to minimize absorption during use.

INDICATIONS AND USAGE

• Sterile Water for Irrigation, USP, is indicated for use as an irrigating fluid for washing, rinsing, and dilution procedures in animals where the use of a sterile, nonpyrogenic, solute-free solution is appropriate. For irrigation only. Not for injection. For veterinary use only.

CONTRAINDICATIONS

• Sterile Water for Irrigation, USP is not for injection.

WARNINGS:

• Sterile Water for Irrigation, USP is hypotonic and may cause hemolysis. It is not recommended for use during surgical procedures. Single-use container. Discard any unused portion promptly after opening to minimize the risk of contamination or pyrogen formation. Inspect solution before use. See Instructions for Use.The container label bears the statement: This solution is hemolytic and may cause hemolysis. See package insert for complete warnings. Keep out of the reach of children

PRECAUTIONS

• Inspect solution before use. See Instructions for Use.
• To minimize the risk of incompatibilities when mixing with additives, inspect the final solution for cloudiness or precipitation immediately after mixing, before administration, and periodically during use.
• Do not use if the product is expired, the lot number is missing or illegible.
• Maintain aseptic conditions

USE IN PREGNANT OR LACTATING ANIMALS:
The safety of Sterile Water for Irrigation, USP has not been established in pregnant or lactating animals. Use only when the potential benefits justify the potential risks. Veterinarian discretion is advised. A documented risk-benefit assessment is recommended.

ADVERSE EVENT REPORTING
To report suspected adverse reactions, contact Vedco Inc. at (888) 708-3326 or report to the FDA at 1-888-FDA-VETS or online at www.fda.gov/reportanimalae

ADVERSE REACTIONS

If an adverse reaction does occur, discontinue the irrigation, evaluate the patient, institute appropriate therapeutic countermeasures and save the remainder of the fluid for examination if deemed necessary. Reported adverse reactions include: Hemolysis due to hypotonicity. Hyponatremia and associated neurological symptoms. Neurological signs such as tremors or seizures may occur secondary to hyponatremia. Fluid overload leading to pulmonary edema.

OVERDOSAGE

Excessive absorption of Sterile Water for Irrigation, USP, particularly when used under pressure or in large volumes, may result in water intoxication, hyponatremia, hypoosmolality, and fluid overload. Clinical signs may include lethargy, weakness, ataxia, altered mentation, tremors, seizures, or respiratory distress. In severe cases, coma or death may occur. If clinically significant absorption is suspected, discontinue irrigation immediately and initiate appropriate corrective measures such as electrolyte monitoring, fluid restriction, and supportive care. Monitor serum electrolytes, fluid balance, and provide supportive care. In severe cases, consider diuretics, dialysis or other interventions as directed by a veterinarian. [see Warnings and Precautions for additional information]

DOSAGE AND ADMINISTRATION

- • This is a single-use container. See Instructions for Use for inspection guidelines.
  • Use only as directed by a veterinarian. Typical irrigation volumes range from 50 mL to 1000 mL depending on the size of the cavity or wound and the nature of the procedure.
  • Inspect the solution visually for particulate matter and discoloration prior to administration, whenever solution and container permit
  • The dose is dependent upon the capacity or surface area of the structure to be irrigated and the nature of the procedure. When used as a diluent or vehicle for drugs, the manufacturer’s recommendations should be followed
  • Administer slowly and avoid excessive pressure to minimize the risk of fluid absorption
  • Aseptic technique must be used throughout handling and administration
  • If additives are introduced, use aseptic technique and mix thoroughly
  • Do not store any solution containing additives. See Shelf Life for disposal instructions.

HOW SUPPLIED

Sterile water for irrigation, USP solution is available in the following sizes:

BOTTLES NDC#

Sterile Water for irrigation,1000 mL NDC 72483-208-02

Sterile Water for irrigation, 500 mL NDC 72483-208-01

INSTRUCTIONS FOR USE:

PLASTIC BOTTLE:
NOTE: Before use, perform the following checks:
• Read the label. Verify the solution composition, lot number, and expiration date on the container.
• Do not use if the product is expired, the lot number is missing or illegible, or if the solution is cloudy or contains a precipitate.
• Invert the container and inspect in good light for leaks or particulate matter. If leaks are found or the seal is not intact, discard the solution.
• Use only if the solution is clear and the container and seals are intact.

PREPARATION FOR ADMINISTRATION:
1. Use aseptic technique when preparing and handling the container.
2. Outer Closure Removal – Grasp the container with one hand and turn the breakaway ring counterclockwise with the other hand until slight resistance is felt.
3. Then, twisting the container in the opposite direction, turn the breakaway ring sharply until the entire outer cap is loose and can be lifted off.
4. Remove screw cap and pour.
5. Once opened, use immediately and discard any unused portion.

INTRODUCTION OF ADDITIVES:
Warning: Some additives may be incompatible.

Known incompatible additives include:
· Strong oxidizing agents
· Alcohol-containing solutions
· Solutions with high electrolyte concentrations
Always verify compatibility before mixing. If incompatibility is suspected, do not use the mixture.

To Add Medication Before Solution Administration.
1. If additives are introduced, follow aseptic technique as described above.
2. Mix solution and medication thoroughly before use.

NOTE: See full directions accompanying the administration set.

STORAGE

- Store at a temperature not higher than 30ºC (86ºF). Avoid excessive heat. Protect from freezing.

CAUTION: Federal law (USA) restricts this drug to use by or on the order of a licensed veterinarian

Manufactured by:
LABORATORIOS ALFA S.R.L
Santo Domingo, Dominican Republic
www.laboratoriosalfa.com
+1-809-544-0222
Toll Free: +1-800-969-0581
Made in Dominican Republic

PACKAGE INSERT

For Animal Use Only

0.9% Sodium Chloride For Irrigation (Bottles)

For Veterinary Use Only

Sterile Water for Irrigation, 500 mL NDC 72483-208-01

Sterile Water for Irrigation,1000 mL NDC 72483-208-02